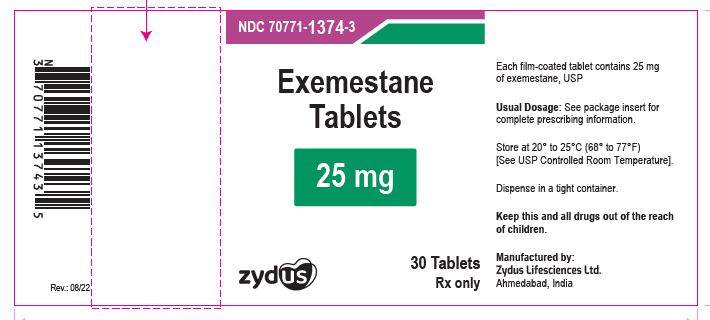 DRUG LABEL: Exemestane
NDC: 70771-1374 | Form: TABLET
Manufacturer: Zydus Lifesciences Limited
Category: prescription | Type: HUMAN PRESCRIPTION DRUG LABEL
Date: 20241128

ACTIVE INGREDIENTS: EXEMESTANE 25 mg/1 1
INACTIVE INGREDIENTS: HYPROMELLOSES; MAGNESIUM CARBONATE; MAGNESIUM STEARATE; MANNITOL; CELLULOSE, MICROCRYSTALLINE; POLYSORBATE 80; SODIUM STARCH GLYCOLATE TYPE A POTATO; TITANIUM DIOXIDE; SILICON DIOXIDE; CROSPOVIDONE; POLYETHYLENE GLYCOL 300

EXEMESTANE TABLETS

PACKAGE LABEL.PRINCIPAL DISPLAY PANEL

NDC 70771-1374-3 in bottle of 30 tablets

Exemestane Tablets, 25 mg

Rx only

30 tablets